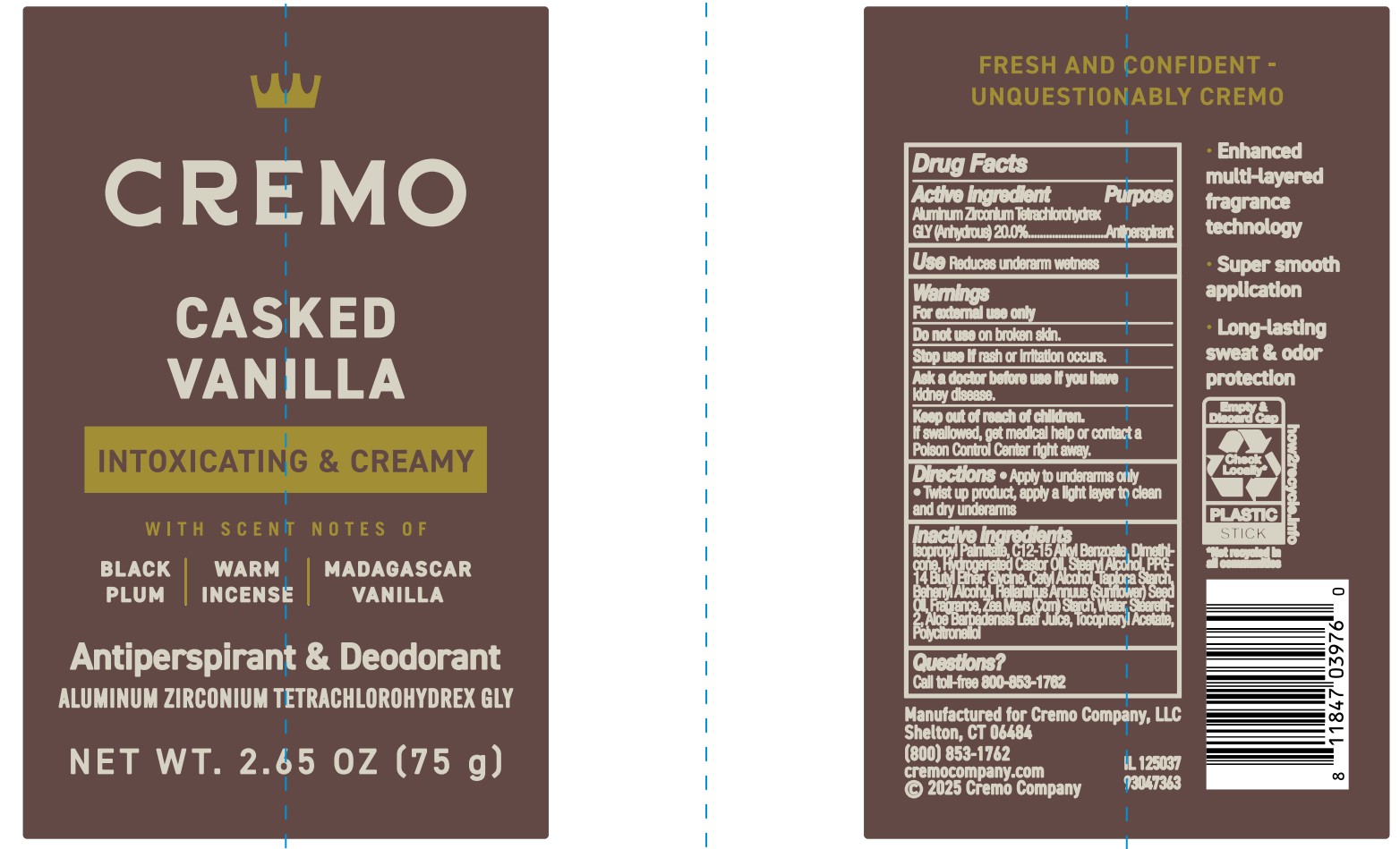 DRUG LABEL: Cremo Company
NDC: 71825-961 | Form: STICK
Manufacturer: Cremo Company
Category: otc | Type: HUMAN OTC DRUG LABEL
Date: 20251202

ACTIVE INGREDIENTS: ALUMINUM ZIRCONIUM TETRACHLOROHYDREX GLY 20 g/100 mL
INACTIVE INGREDIENTS: PPG-14 BUTYL ETHER; HYDROGENATED CASTOR OIL; ZEA MAYS (CORN) STARCH; ALOE BARBADENSIS LEAF JUICE; CETYL ALCOHOL; WATER; C12-15 ALKYL BENZOATE; DIMETHICONE; BEHENYL ALCOHOL; .ALPHA.-TOCOPHEROL ACETATE; ISOPROPYL PALMITATE; HELIANTHUS ANNUUS (SUNFLOWER) SEED OIL; STEARYL ALCOHOL; STEARETH-2; TAPIOCA STARCH; GLYCINE

Active ingredient

Aluminum Zirconium Tetrachlorohydrex GLY (Anhydrous) (20.0%)

Purpose

Antiperspirant

Use

reduces underarm wetness

Warnings

For external use only

Do not use

on broken skin.

Stop use if

skin rash or irritation occurs.

Ask a doctor before use if you have

kidney disease.

Keep out of reach of children.

If swallowed, get medical help or contact a Poison Control Center right away.

Directions

• Apply to underarms only. • Twist up product, apply a light layer to clean and dry underarms

Inactive ingredients

Isopropyl Palmitate, C12-15 Alkyl Benzoate, Dimethicone, Hydrogenated Castor Oil, Stearyl Alcohol, PPG-14 Butyl Ether, Glycine, Cetyl Alcohol, Tapioca Starch, Behenyl Alcohol, Helianthus Annuus (Sunflower) Seed Oil, Fragrance, Zea Mays (Corn) Starch, Water, Steareth-2, Aloe Barbadensis Leaf Juice, Tocopheryl Acetate, Polycitronellol

Questions

Call toll-free 800-853-1762

PACKAGE LABEL

Cremo
CASKED VANILLA
INTOXICATING & CREAMY
WITH SCENT NOTES OF
BLACK PLUM| WARM INCENSE | MADAGASCAR VANILLA
Antiperspirant & Deodorant
ALUMINUM ZIRCONIUM TETRACHLOROHYDREX GLY
NET WT. 2.65 OZ (75 g)